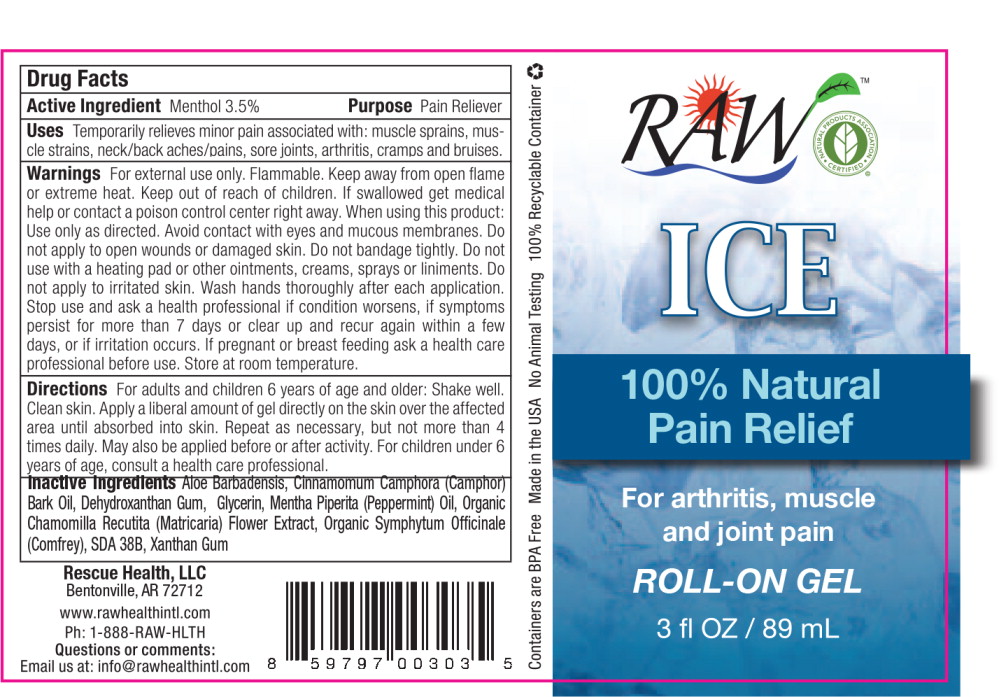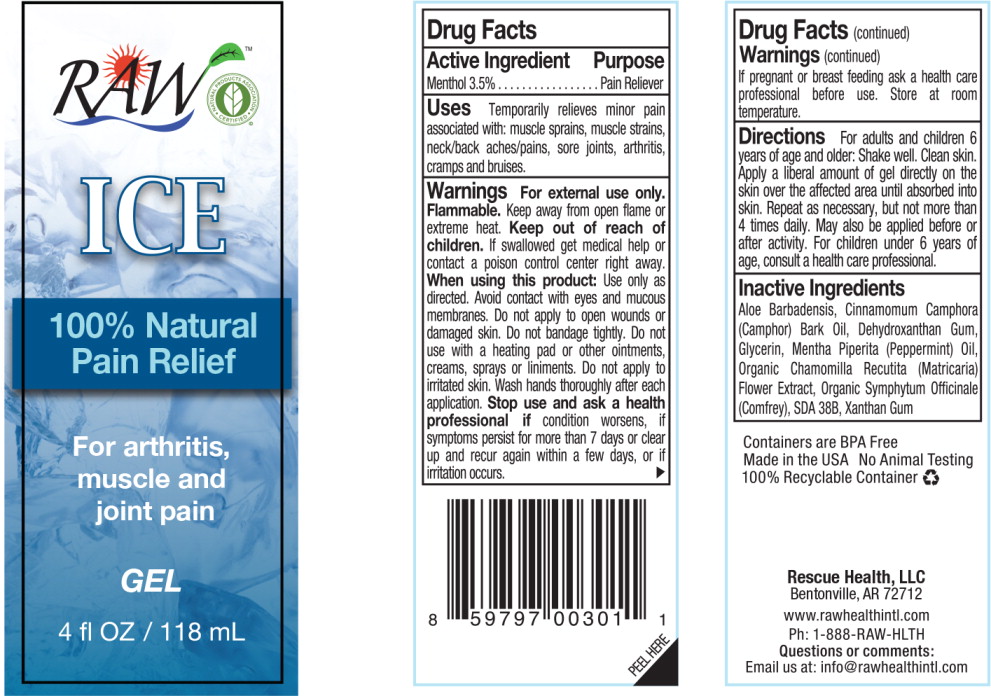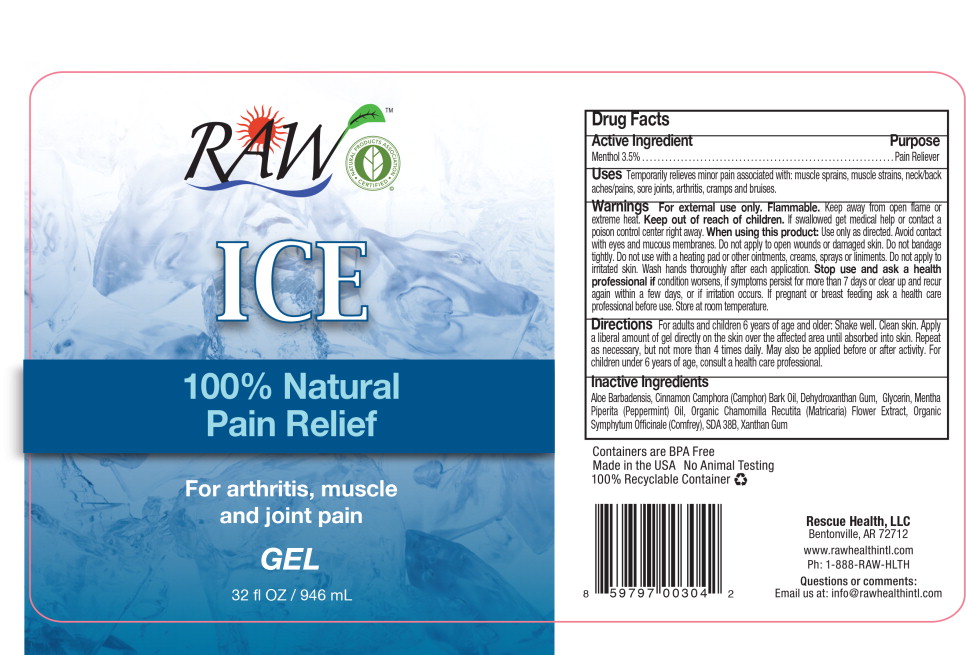 DRUG LABEL: Raw Ice
NDC: 69381-2500 | Form: GEL
Manufacturer: Rescue Dog Health
Category: otc | Type: HUMAN OTC DRUG LABEL
Date: 20141218

ACTIVE INGREDIENTS: menthol 3.5 mg/1 L
INACTIVE INGREDIENTS: aloe vera leaf; glycerin; peppermint oil; xanthan gum; camphor oil; matricaria recutita; symphytum uplandicum leaf

Drug Facts

Active Ingredient

Menthol 3.5%

Purpose

Pain Reliever

Uses

Temporarily relieves minor pain associated with: muscle sprains, muscle strains, neck/back aches/pains, sore joints, arthritis, cramps and bruises.

Warnings

KEEP OUT OF REACH OF CHILDREN

For external use only. Flammable. Keep away from open flame or extreme heat. Keep out of reach of children. If swallowed get medical help or contact a poison control center right away. When using this product: Use only as directed. Avoid contact with eyes and mucous membranes. Do not apply to open wounds or damaged skin. Do not bandage tightly. Do not use with a heating pad or other ointments, creams, sprays or liniments. Do not apply to irritated skin. Wash hands thoroughly after each application. Stop use and ask a health professional if condition worsens, if symptoms persist for more than 7 days or clear up and recur again within a few days, or if irritation occurs. If pregnant or breast feeding ask a health care professional before use. Store at room temperature.

Directions

For adults and children 6 years of age and older: Shake well. Clean skin. Apply a liberal amount of gel directly on the skin over the affected area until absorbed into skin. Repeat as necessary, but not more than 4 times daily. May also be applied before or after activity. For children under 6 years of age, consult a health care professional.

Inactive Ingredients

Aloe Barbadensis, Cinnamomum Camphora (Camphor) Bark Oil, Dehydroxanthan Gum, Glycerin, Mentha Piperita (Peppermint) Oil, Organic Chamomilla Recutita (Matricaria) Flower Extract, Organic Symphytum Officinale (Comfrey), SDA 38B, Xanthan Gum

Rescue Health, LLC
Bentonville, AR 72712

www.rawhealthintl.com
Ph: 1-888-RAW-HLTH

Questions or comments:

Email us at: info@rawhealthintl.com

Principal Display Panel - Bottle Label

RAW™

ICE

100% Natural
Pain Relief

For arthritis, muscle
and joint pain

ROLL-ON GEL

3 fl OZ/89 mL

Principal Display Panel - Bottle Label

RAW™

ICE

100% Natural
Pain Relief

For arthritis,
muscle and
joint pain

GEL

4 fl OZ/118 mL

Principal Display Panel - Bottle Label

RAW™

ICE

100% Natural
Pain Relief

For arthritis, muscle
and joint pain

GEL

32 fl OZ/946 mL